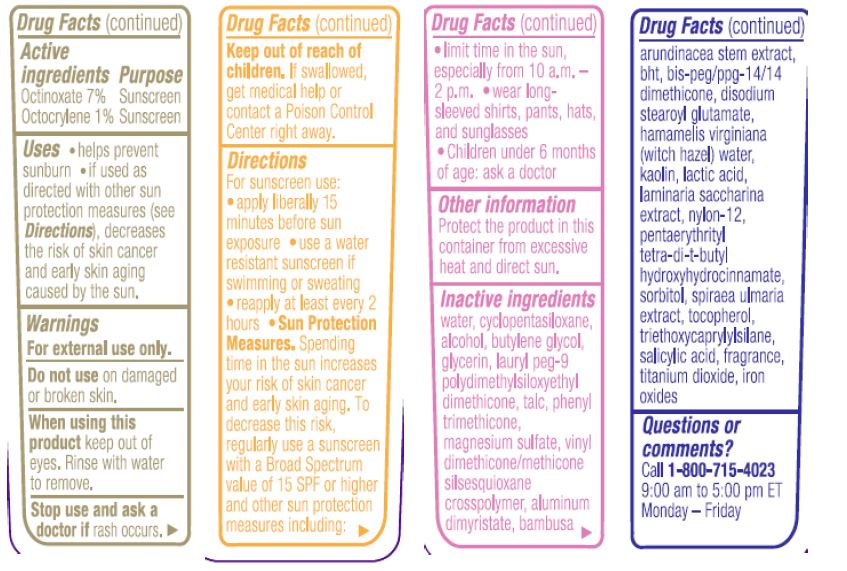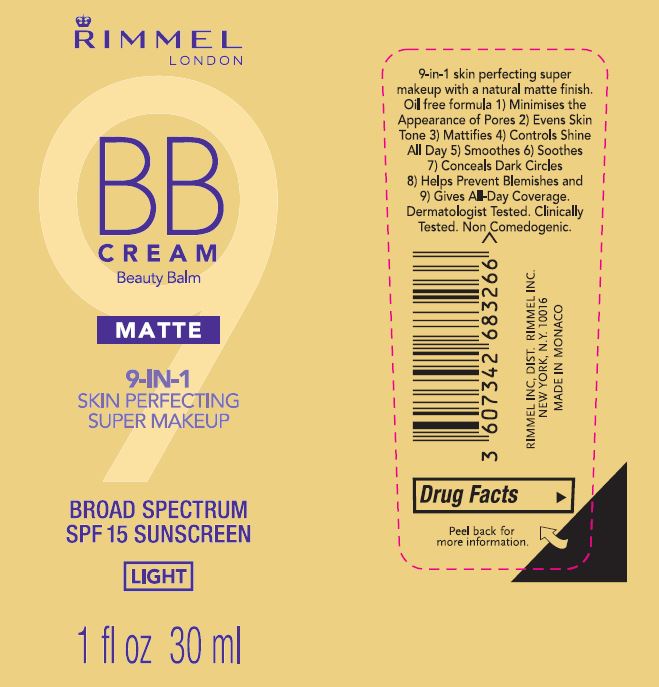 DRUG LABEL: Rimmel BB Cream Beauty Balm Matte 9-IN-1 Skin Perfecting Super Makeup SPF 15
NDC: 76485-1113 | Form: CREAM
Manufacturer: Rimmel Inc
Category: otc | Type: HUMAN OTC DRUG LABEL
Date: 20201105

ACTIVE INGREDIENTS: OCTOCRYLENE 1 g/100 mL; OCTINOXATE 7 g/100 mL
INACTIVE INGREDIENTS: TOCOPHEROL; FERRIC OXIDE RED; PHENYL TRIMETHICONE; PENTAERYTHRITOL TETRAKIS(3-(3,5-DI-TERT-BUTYL-4-HYDROXYPHENYL)PROPIONATE); BUTYLENE GLYCOL; GLYCERIN; NYLON-12; BUTYLATED HYDROXYTOLUENE; WATER; MAGNESIUM SULFATE, UNSPECIFIED; TALC; HAMAMELIS VIRGINIANA TOP WATER; LAURYL PEG-9 POLYDIMETHYLSILOXYETHYL DIMETHICONE; CYCLOMETHICONE 5; LACTIC ACID; ALCOHOL; SACCHARINA LATISSIMA THALLUS; SORBITOL; TRIETHOXYCAPRYLYLSILANE; SALICYLIC ACID; DISODIUM STEAROYL GLUTAMATE; BIS-PEG/PPG-14/14 DIMETHICONE; TITANIUM DIOXIDE; FILIPENDULA ULMARIA ROOT; BAMBUSA ARUNDINACEA STEM; VINYL DIMETHICONE/METHICONE SILSESQUIOXANE CROSSPOLYMER; ALUMINUM DIMYRISTATE; KAOLIN

Rimmel BB Cream Beauty Balm Matte 9-IN-1 Skin Perfecting Super Makeup SPF15

Active ingredients

Octinoxate 7%

Octocrylene

Purpose

Sunscreen

Uses

helps prevent sunburn.

if used as directed with other sun protection measures (see Directions), decreases the risk of skin cancer and early skin aging caused by the sun.

WARNINGS

For external use only.

Do not use on damaged or broken skin.

When using this product keep out of eyes. Rinse with water to remove.

Stop use and ask a doctor if rash occurs.

Keep out of reach of children. If swallowed, get medical help or contact a Poison Control Center right away.

Directions

For sunscreen use:

Apply liberally 15 minutes before sun exposure

use a water resistant sunscreen if swimming or sweating

reapply at least every 2 hours

Sun Protection Measures. Spending time in the sun increases your risk of skin cancer and early skin aging. To decrease this risk, regularly use a sunscreen with a Broad Spectrum value of 15 SPF or higher and other sun protection measures including: limit time in the sun, especially from 10 a.m.- 2 p.m. wear longsleeved shirts, pants, hats, and sunglasses. Children under 6 months of age: ask a doctor

Other information

Protect the product in this container from excessive heat and direct sun.

Quesitons or Comments?

Call 1-800-715-4023 9:00 am to 5:00 pm ET Monday-Friday

Principal Display Panel

Rimmel London

BB Cream

Beauty Balm

MATTE

9-IN-1 SKIN PERFECTING SUPER MAKEUP

BROAD SPECTRUM

SPF 15 SUNSCREEN

LIGHT

1 fl oz 30 ml